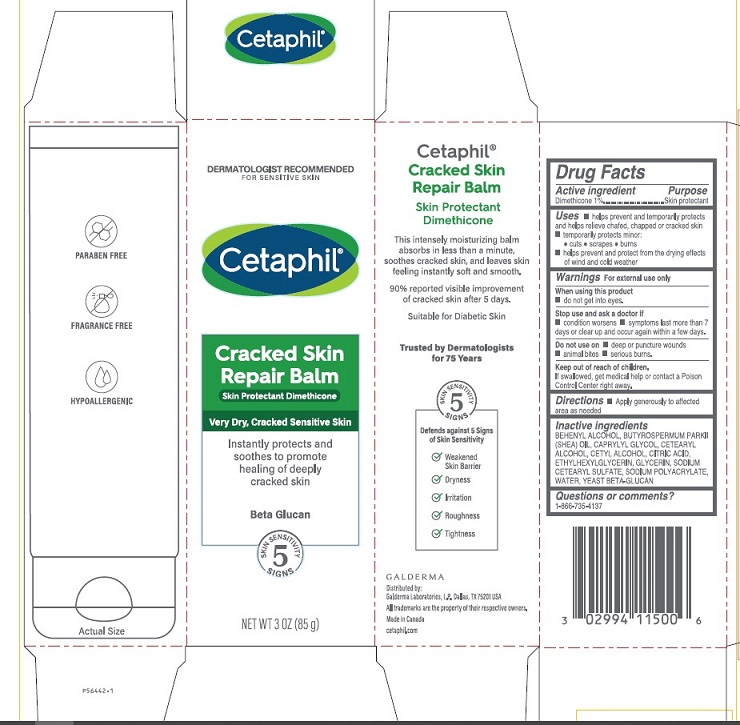 DRUG LABEL: Cetaphil Cracked Skin Repair Balm
NDC: 0299-4115 | Form: CREAM
Manufacturer: Galderma Laboratories, L.P.
Category: otc | Type: HUMAN OTC DRUG LABEL
Date: 20231130

ACTIVE INGREDIENTS: Dimethicone 10 mg/1 g
INACTIVE INGREDIENTS: Docosanol; Sheanut Oil; Caprylyl Glycol; Cetostearyl Alcohol; Cetyl Alcohol; Citric Acid Monohydrate; Ethylhexylglycerin; Glycerin; Sodium Cetostearyl Sulfate; Sodium Polyacrylate (2500000 Mw); Water

Drug Facts

Active ingredient......Purpose

Dimethicone 1%......Skin Protectant

Uses

● helps prevent and temporarily protects and helps relieve chafed, chapped or cracked skin
● temporary protects minor:
● cuts ● scrapes ● burns
● helps prevent and protect from the drying effects of wind and cold weather

Warnings

For external use only.

When using this product ● Do not get into eyes.

Stop use and ask a Doctor if ● condition worsens ● symptoms last more than 7 days or clear up and occur again within a few days.

Do not use on ● deep or puncture wounds ● animal bites ● serious burns

Keep out of reach of children. If swallowed, get medical help or contact a Poison Control Center right away.

Directions

● Apply generously to affected area as needed

Inactive Ingredients

BEHENYL ALCOHOL, BUTYROSPERMUM PARKII (SHEA) OIL, CAPRYLYL GLYCOL, CETEARYL ALCOHOL, CETYL ALCOHOL, CITRIC ACID, ETHYLHEXYLGLYCERIN, GLYCERIN, SODIUM CETEARYL SULFATE, SODIUM POLYACRYLATE, WATER, YEAST BETAGLUCAN

Questions or comments?

1-866-735-4137

Distributed By:
Galderma Laboratories, L.P.
Dallas, TX 75201 USA

All trademarks are the property of their respective owners

Made in Canada

cetaphil.com

PRINCIPLE DISPLAY PANEL - 3 oz carton

Dermatologist Recommended
For Sensitive Skin
Cetaphil®

Cracked Skin
Repair Balm
Skin Protectant Dimethicone

Very Dry, Cracked Sensitive Skin

Instantly protects and
soothes to promote
healing of deeply
cracked skin
Beta Glucan

5 skin sensitivity signs

NET WT 3 OZ (85 g)
P56442-1